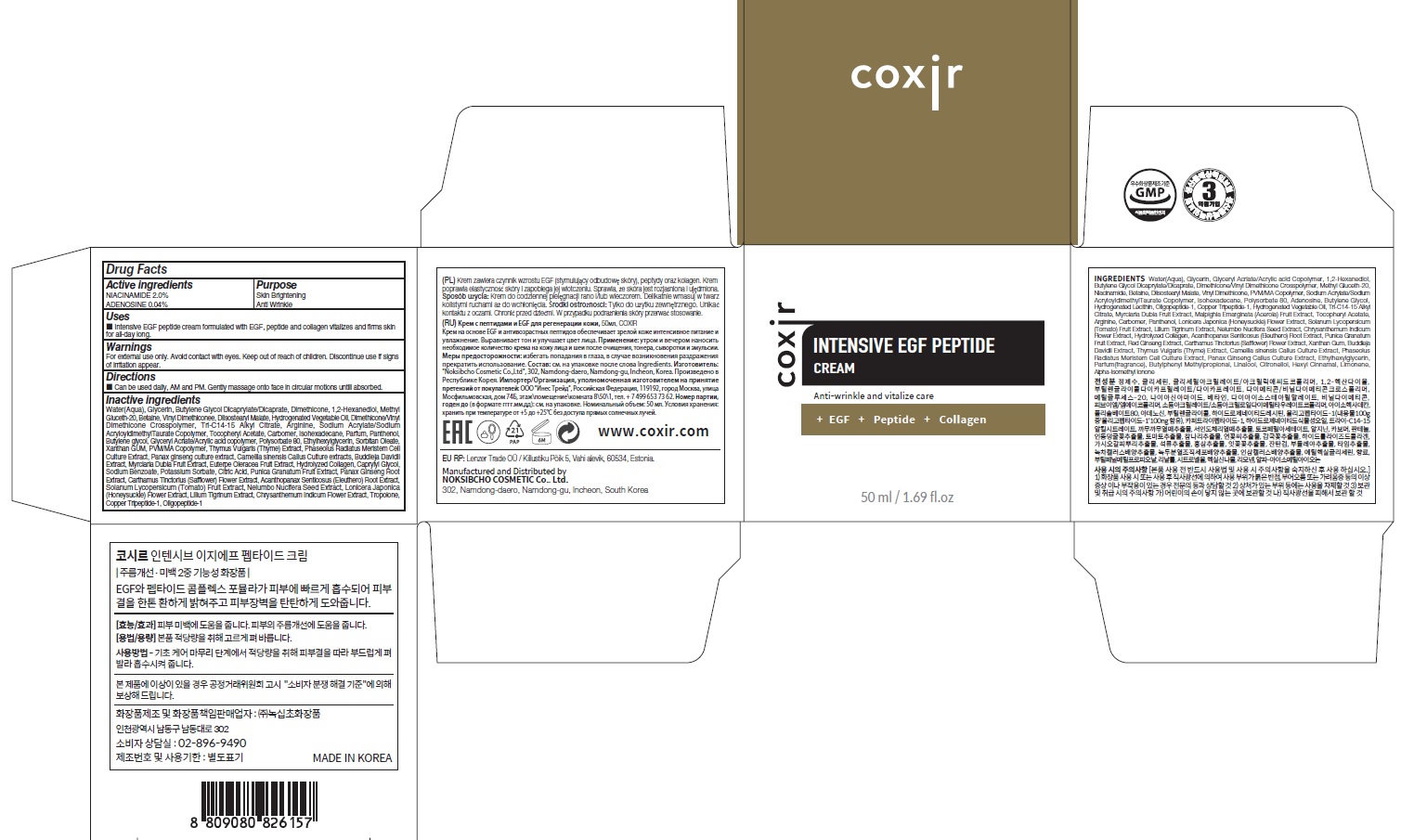 DRUG LABEL: COXIR INTENSIVE EGF PEPTIDE
NDC: 73590-0071 | Form: CREAM
Manufacturer: NOKSIBCHO cosmetic Co., Ltd.
Category: otc | Type: HUMAN OTC DRUG LABEL
Date: 20210714

ACTIVE INGREDIENTS: NIACINAMIDE 1.0 g/50 mL; ADENOSINE 0.02 g/50 mL
INACTIVE INGREDIENTS: Water; Glycerin; Butylene Glycol

Drug Facts

ACTIVE INGREDIENTS

NIACINAMIDE 2.0%
ADENOSINE 0.04%

INACTIVE INGREDIENTS

Water(Aqua), Glycerin, Butylene Glycol Dicaprylate/Dicaprate, Dimethicone, 1,2-Hexanediol, Methyl Gluceth-20, Betaine, Vinyl Dimethiconee, Diisostearyl Malate, Hydrogenated Vegetable Oil, Dimethicone/Vinyl Dimethicone Crosspolymer, Tri-C14-15 Alkyl Citrate, Arginine, Sodium Acrylate/Sodium AcryloyldimethylTaurate Copolymer, Tocopheryl Acetate, Carbomer, Isohexadecane, Parfum, Panthenol, Butylene glycol, Glyceryl Acrlate/Acrylic acid copolymer, Polysorbate 80, Ethylhexylglycerin, Sorbitan Oleate, Xanthan GUM, PVM/MA Copolymer, Thymus Vulgaris (Thyme) Extract, Phaseolus Radiatus Meristem Cell Culture Extract, Panax ginseng culture extract, Camellia sinensis Callus Culture extracts, Buddleja Davidii Extract, Myrciaria Dubia Fruit Extract, Euterpe Oleracea Fruit Extract, Hydrolyzed Collagen, Caprylyl Glycol, Sodium Benzoate, Potassium Sorbate, Citric Acid, Punica Granatum Fruit Extract, Panax Ginseng Root Extract, Carthamus Tinctorius (Safflower) Flower Extract, Acanthopanax Senticosus (Eleuthero) Root Extract, Solanum Lycopersicum (Tomato) Fruit Extract, Nelumbo Nucifera Seed Extract, Lonicera Japonica (Honeysuckle) Flower Extract, Lilium Tigrinum Extract, Chrysanthemum Indicum Flower Extract, Tropolone, Copper Tripeptide-1, Oligopeptide-1

PURPOSE

Skin Brightening
Anti wrinkle

WARNINGS

For external use only.
Avoid contact with eyes.
Keep out of reach of children.
Discontinue use if signs of irritation appear.

KEEP OUT OF REACH OF CHILDREN

Uses

■ Intensive EGF peptide cream formulated with EGF, peptide and collagen vitalizes and firms skin for all-day long.

Directions

■ Can be used daily, AM and PM. Gently massage onto face in circular motions untill absorbed.